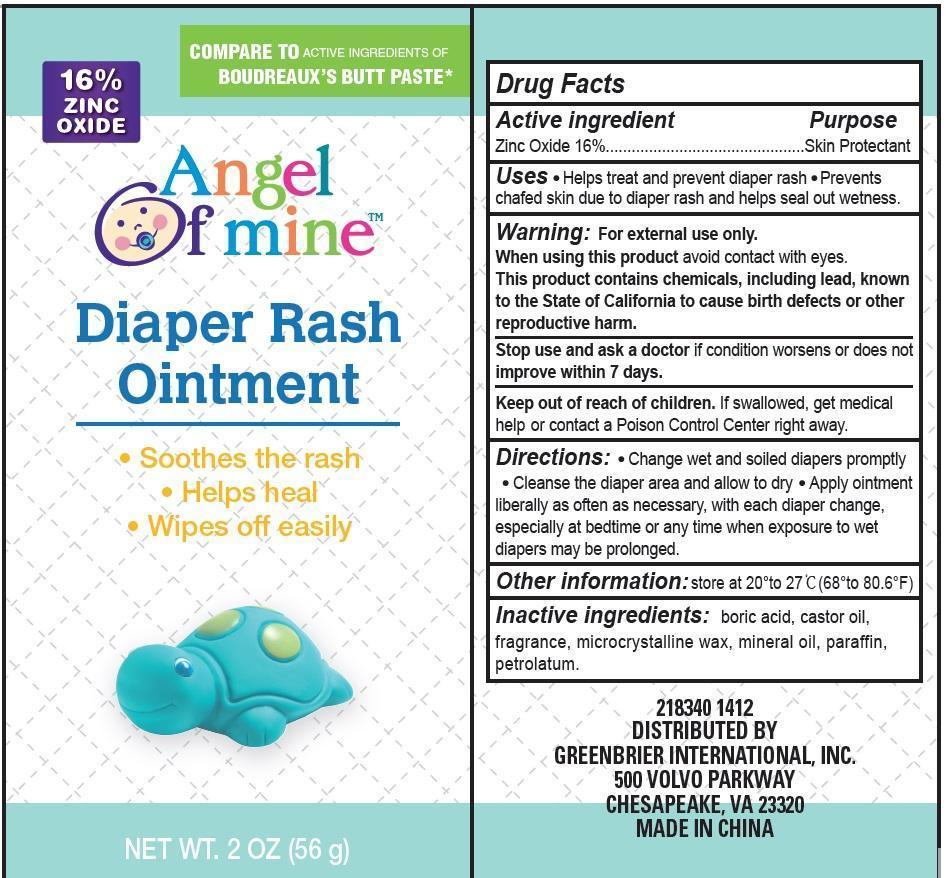 DRUG LABEL: Angel of mine Diaper Rash
NDC: 58638-002 | Form: OINTMENT
Manufacturer: Wenzhou Senos Cosmetics Technology Co., Ltd.
Category: otc | Type: HUMAN OTC DRUG LABEL
Date: 20170522

ACTIVE INGREDIENTS: ZINC OXIDE 160 mg/1 g
INACTIVE INGREDIENTS: BORIC ACID; CASTOR OIL; MICROCRYSTALLINE WAX; MINERAL OIL; PARAFFIN; PETROLATUM

Diaper Rash

Drug Facts

Active ingredient

Zinc Oxide 16%

Purposes

Skin Protectant

Uses

- Helps treat and prevent diaper rash
- Prevents chafed skin due to diaper rash
- Helps seal out wetness

Warnings

For external use only.

When using this product

- avoid contact wih eyes
- this product contains chemicals, including lead, known to the State of California to case birth defects or othr reproductive harm

Stop use and ask a doctor if

- Condition worsens
- or does not improve within 7 days

Keep out of reach of children. If swallowed, get medical help or contact a Poison Control Center right away.

Directions

- Change wet or soiled diapers promptly
- Clean the diaper area and allow to dry
- Apply iubtnebt liberally as often as necessary, with each diaper change, especially at bedtime or any time prolonged exposure to wet diapers may be prolonged.

Inactive ingredients

boric acid, castor ol, fragrance, microcrystalline wax, mineral oil, paraffin, petrolatum

PRINCIPAL DISPLAY PANEL

Angel of mine™
diaper rash Ointment

- Soothes the rash
- Helps heal
- Wipes of easily

Net Wt. 2 oz. (56g)